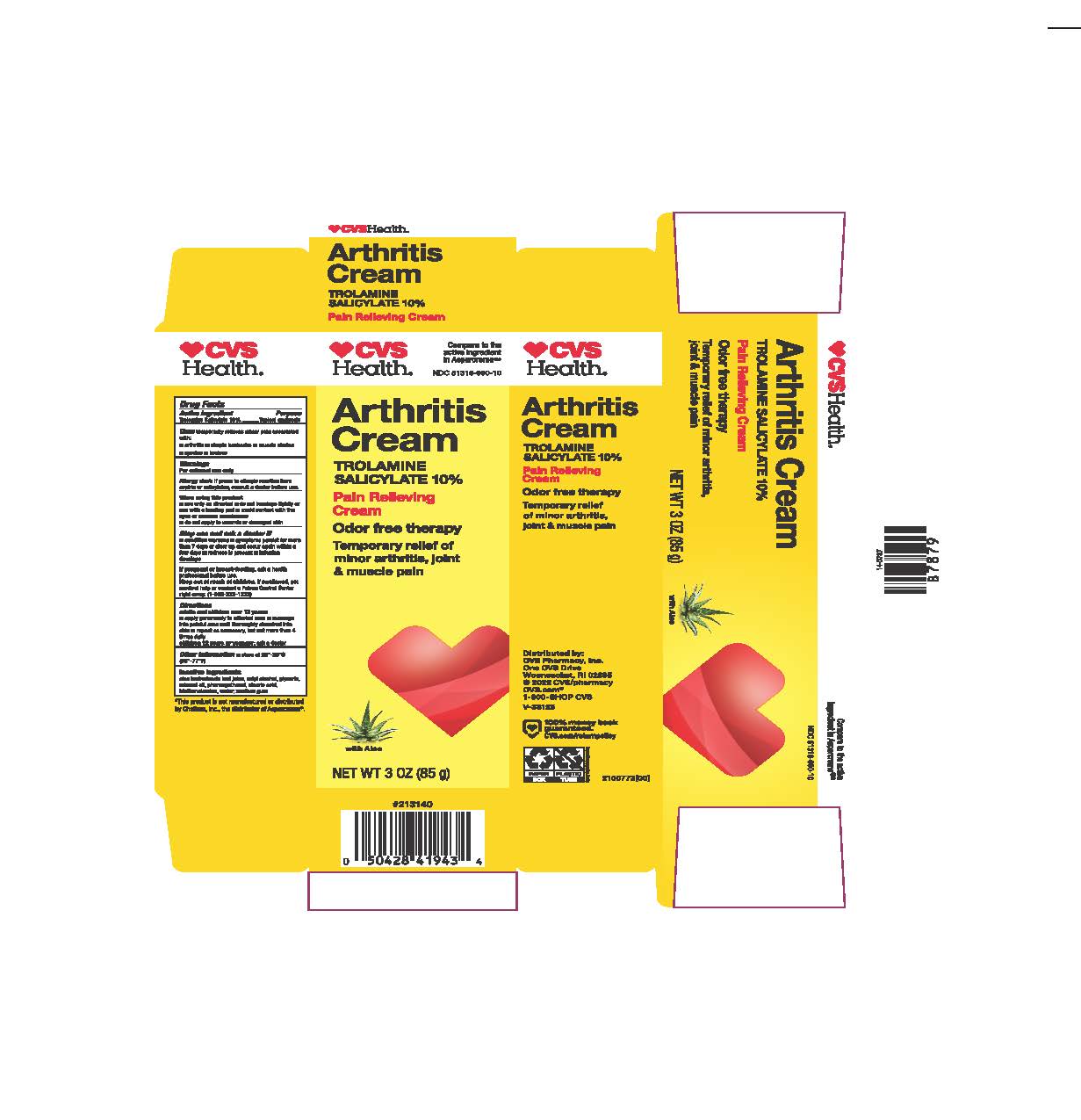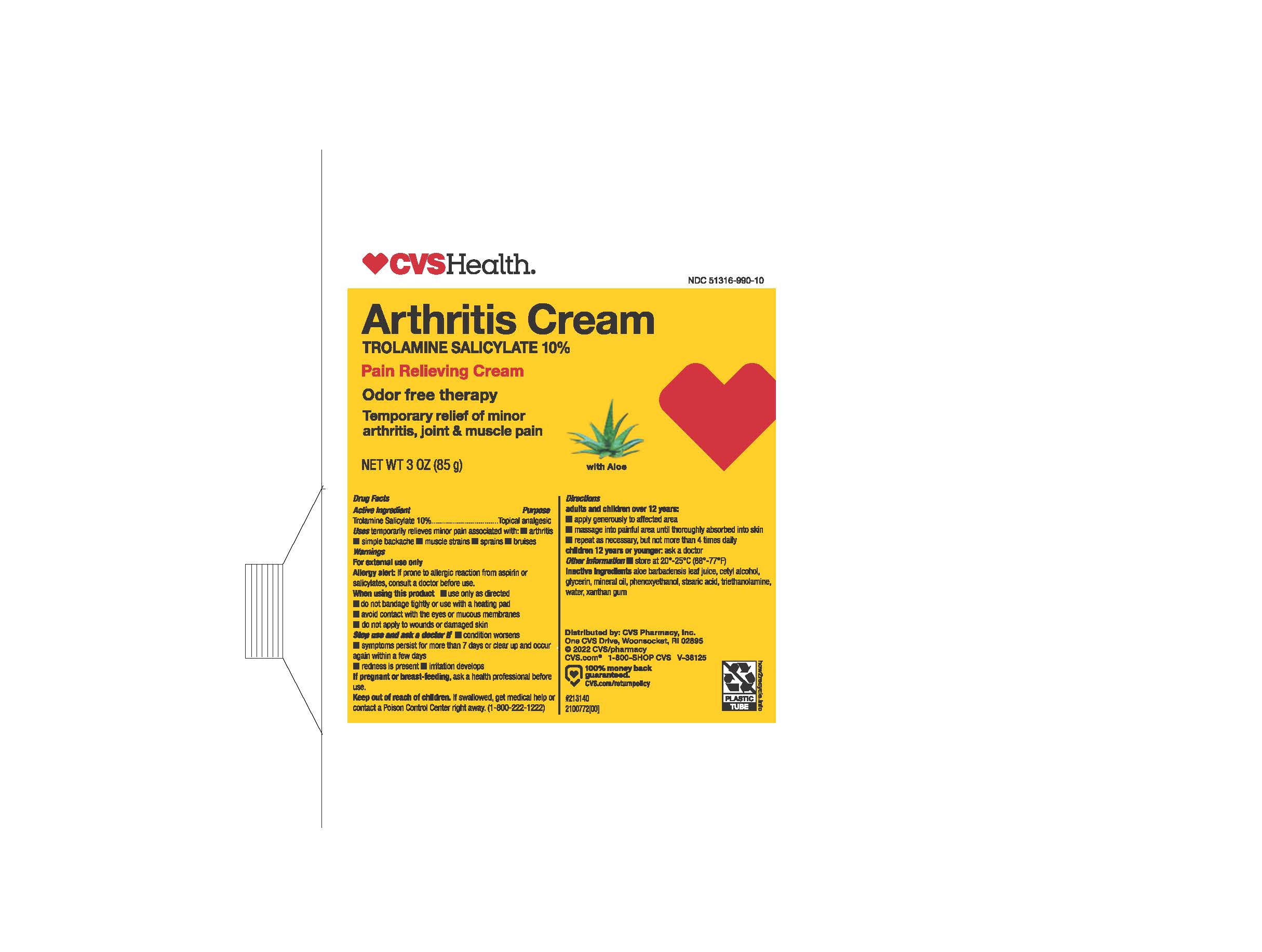 DRUG LABEL: Arthritis Cream
NDC: 51316-990 | Form: CREAM
Manufacturer: CVS
Category: otc | Type: HUMAN OTC DRUG LABEL
Date: 20241211

ACTIVE INGREDIENTS: TROLAMINE SALICYLATE 10 g/100 g
INACTIVE INGREDIENTS: MINERAL OIL; ALOE VERA LEAF; WATER; XANTHAN GUM; GLYCERIN; CETYL ALCOHOL; STEARIC ACID; TROLAMINE; PHENOXYETHANOL

CVS Arthritis Cream

ACTIVE INGREDIENT

Trolamine Salicylate 10%

PURPOSE

Topical analgesic

INDICATIONS AND USAGE

Temporarily relieves minor pain associated with:

Arthritis

Simple backache

muscle strains

sprains

bruises

WARNINGS

For external use only

Allergy Alert:

If prone to allergic reaction from aspirin or salicylates, consult a doctor before use.

When using the product

use only as directed

do not bandage tightly or use with a heating pad

avoid contact with eyes or mucous membranes

do not apply to wounds or damaged skin

Stop use and ask doctor if

condition worsens

symptoms persist for more than 7 days or clear up and occur again within few days

redness is present

irritation develops

PREGNANCY OR BREAST FEEDING

If pregnant or breast feeding, ask a health professional before use.

Keep out of reach of children. If swallowed, get medical help or contact a Poison Control right away. (1-800-222-1222)

Directions:

adults and children over 12 years:

apply generously to affected area

massage into painful area until thoroughly absorbed into skin

repeat as necessary, but not more than 4 times daily

Children 12 years and younger: ask a doctor

OTHER SAFETY INFORMATION

Store at 20° - 25°C (68° - 77°F)

INACTIVE INGREDIENT

Aloe barbadensis leaf juice, cetyl alcohol, glycerin, mineral oil, phenoxyethanol, stearic acid, triethanolamine, water, xanthan gum